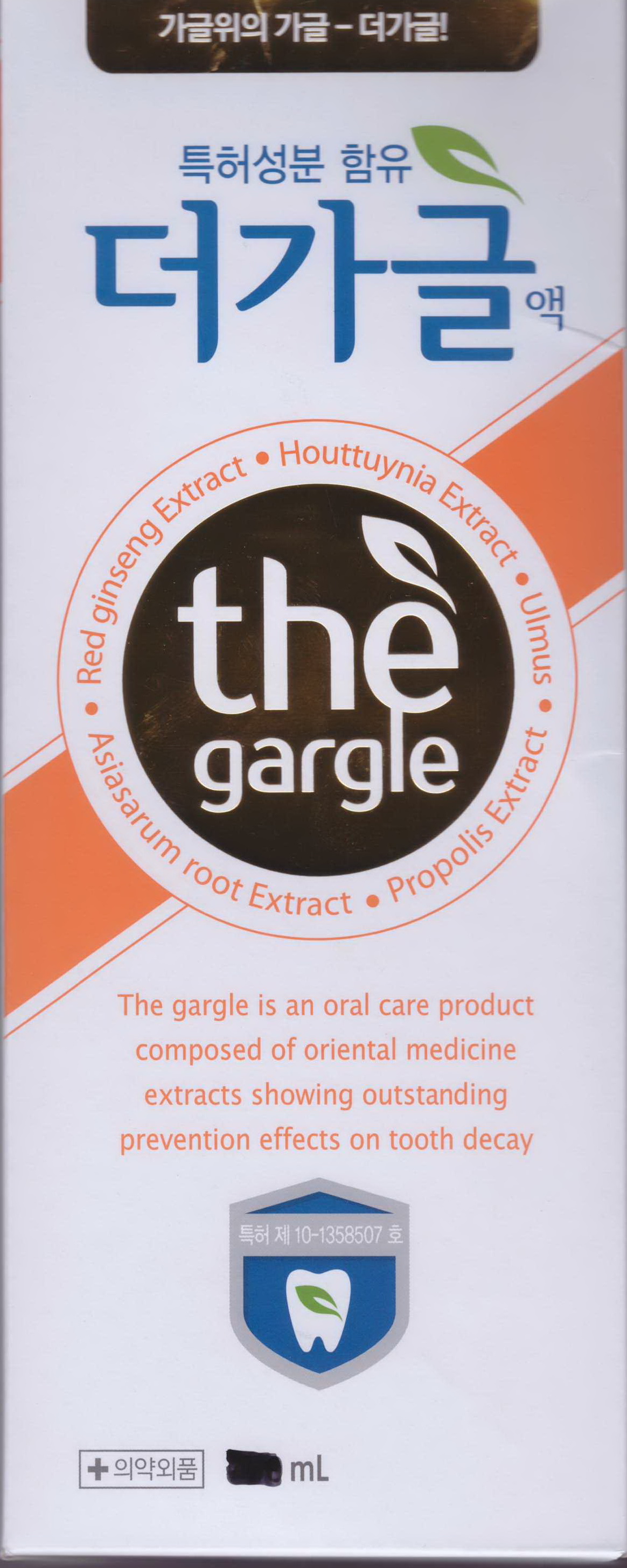 DRUG LABEL: The Gargle
NDC: 41525-7001 | Form: MOUTHWASH
Manufacturer: PBS Co., Ltd.
Category: otc | Type: HUMAN OTC DRUG LABEL
Date: 20150122

ACTIVE INGREDIENTS: SODIUM FLUORIDE 0.02 mg/100 mL
INACTIVE INGREDIENTS: ALLANTOIN; XYLITOL; CITRIC ACID MONOHYDRATE

Drug Facts

ACTIVE INGREDIENT

sodium fluoride

INACTIVE INGREDIENT

purified water, ethyl alcohol, allantoin, glycerin, xylitol, sodium saccharin, green tea, malic acid, lactic acid, sodium benzoate, citric acid peg-40 hydrogenated castor oil, sodium citrate, l-menthol, red ginseng ext, ulmus ext, red ginseng fragrance, mint fragrance, houttuynia ext, propolis ext

PURPOSE

for dental care

keep out of reach of the children

INDICATIONS AND USAGE

① Turn the container cap and open, pour The Gargle into the cap about 10-15ml (not to overflow the cap) and
put into mouth.
② Goggle it thoroughly all over the inner mouth about 10 seconds.
③ After ②, in order to sterilize mouth, hold the liquid in the mouth about 30 seconds and spit out

WARNINGS

do not swallow

for oral administration